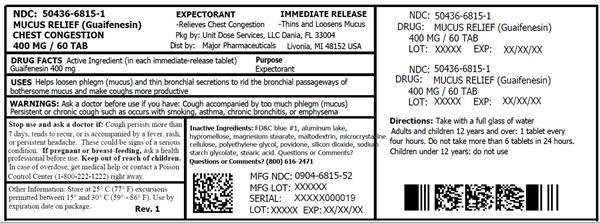 DRUG LABEL: Mucus Relief Chest Congestion
NDC: 50436-6815 | Form: TABLET, FILM COATED
Manufacturer: Unit Dose Services
Category: otc | Type: HUMAN OTC DRUG LABEL
Date: 20190718

ACTIVE INGREDIENTS: GUAIFENESIN 400 mg/1 1
INACTIVE INGREDIENTS: FD&C BLUE NO. 1; HYPROMELLOSE, UNSPECIFIED; MAGNESIUM STEARATE; MALTODEXTRIN; MICROCRYSTALLINE CELLULOSE; POLYETHYLENE GLYCOL, UNSPECIFIED; POVIDONE, UNSPECIFIED; SILICON DIOXIDE; SODIUM STARCH GLYCOLATE TYPE A POTATO; STEARIC ACID

Major 44-532

Active ingredient (in each immediate-release tablet)

Guaifenesin 400 mg

Purpose

Expectorant

Uses

helps loosen phlegm (mucus) and thin bronchial secretions to rid the bronchial passageways of bothersome mucus and make coughs more productive

Warnings

Ask a doctor before use if you have

- cough accompanied by too much phlegm (mucus)
- persistent or chronic cough such as occurs with smoking, asthma, chronic bronchitis, or emphysema

Stop use and ask a doctor if

cough persists more than 7 days, tends to recur, or is accompanied by a fever, rash, or persistent headache. These could be signs of a serious condition.

If pregnant or breast-feeding,

ask a health professional before use.

Keep out of reach of children.

In case of overdose, get medical help or contact a Poison Control Center (1-800-222-1222) right away.

Directions

- take with a full glass of water
- adults and children 12 years and over: 1 tablet every 4 hours. Do not take more than 6 tablets in 24 hours.
- children under 12 years: do not use

Other information

- store at 25ºC (77ºF); excursions permitted between 15º-30ºC (59º-86ºF)
- use by expiration date on package

Inactive ingredients

FD&C blue #1 aluminum lake, hypromellose, magnesium stearate, maltodextrin, microcrystalline cellulose, polyethylene glycol, povidone, silicon dioxide, sodium starch glycolate, stearic acid

Questions or comments?

(800) 616-2471

HOW SUPPLIED

Product: 50436-6815

NDC: 50436-6815-1 60 TABLET, FILM COATED in a BOTTLE